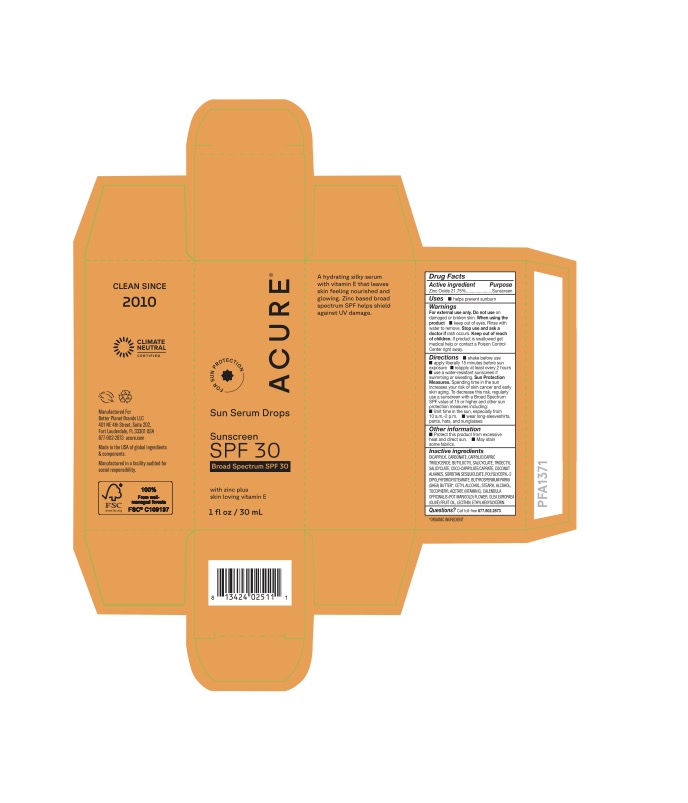 DRUG LABEL: Sun Serum Drops
NDC: 54136-371 | Form: LIQUID
Manufacturer: Better Planet Brands LLC
Category: otc | Type: HUMAN OTC DRUG LABEL
Date: 20251203

ACTIVE INGREDIENTS: ZINC OXIDE 21.8 g/100 g
INACTIVE INGREDIENTS: COCONUT ALKANES; SORBITAN SESQUIOLEATE; STEARYL ALCOHOL; TRIDECYL SALICYLATE; BUTYROSPERMUM PARKII (SHEA) BUTTER; CALENDULA OFFICINALIS FLOWER; SOYBEAN LECITHIN; OLEA EUROPAEA (OLIVE) FRUIT OIL; CETYL ALCOHOL; BUTYLOCTYL SALICYLATE; POLYGLYCERYL-2 DIPOLYHYDROXYSTEARATE; .ALPHA.-TOCOPHEROL ACETATE, D-; COCO-CAPRYLATE/CAPRATE; DICAPRYLYL CARBONATE; ETHYLHEXYLGLYCERIN; CAPRYLIC/CAPRIC TRIGLYCERIDE

Sun Serum Drops

Purpose

Sunscreen

Uses

• helps prevent sunburn

Warnings

• For external use

• Do not use on damaged or broken skin.

• Stop use and ask a doctor if rash occurs.

• Keep out of reach of children.

If product is swallowed get medical help or contact a Poison Control Center right away.

Other information

• Protect this product from excessive heat and direct sun. • May stain some

Inactive Ingredients

DICAPRYLYL CARBONATE, CAPRYLIC/CAPRIC TRIGLYCERIDE, BUTYLOCTYL SALICYCLATE, TRIDECTYL SALICYCLATE, COCO-CAPRYLATE/ CAPRATE, COCONUT ALKANES, SORBITAN SESQUIOLEATE, POLYGLYCERYL-2 DIPOLYHYDROXYSTEARATE, BUTYROSPERMUM PARKII (SHEA) BUTTER*, CETYL ALCOHOL, STEARYL ALCOHOL,

TOCOPHERYL ACETATE (VITAMIN E), CALENDULA OFFICINALIS (POT MARIGOLD) FLOWER, OLEA EUROPEA (OLIVE) FRUIT OIL, LECITHIN, ETHYLHEXYGLYCERIN.

Questions?

Call toll-free 877.902.2873